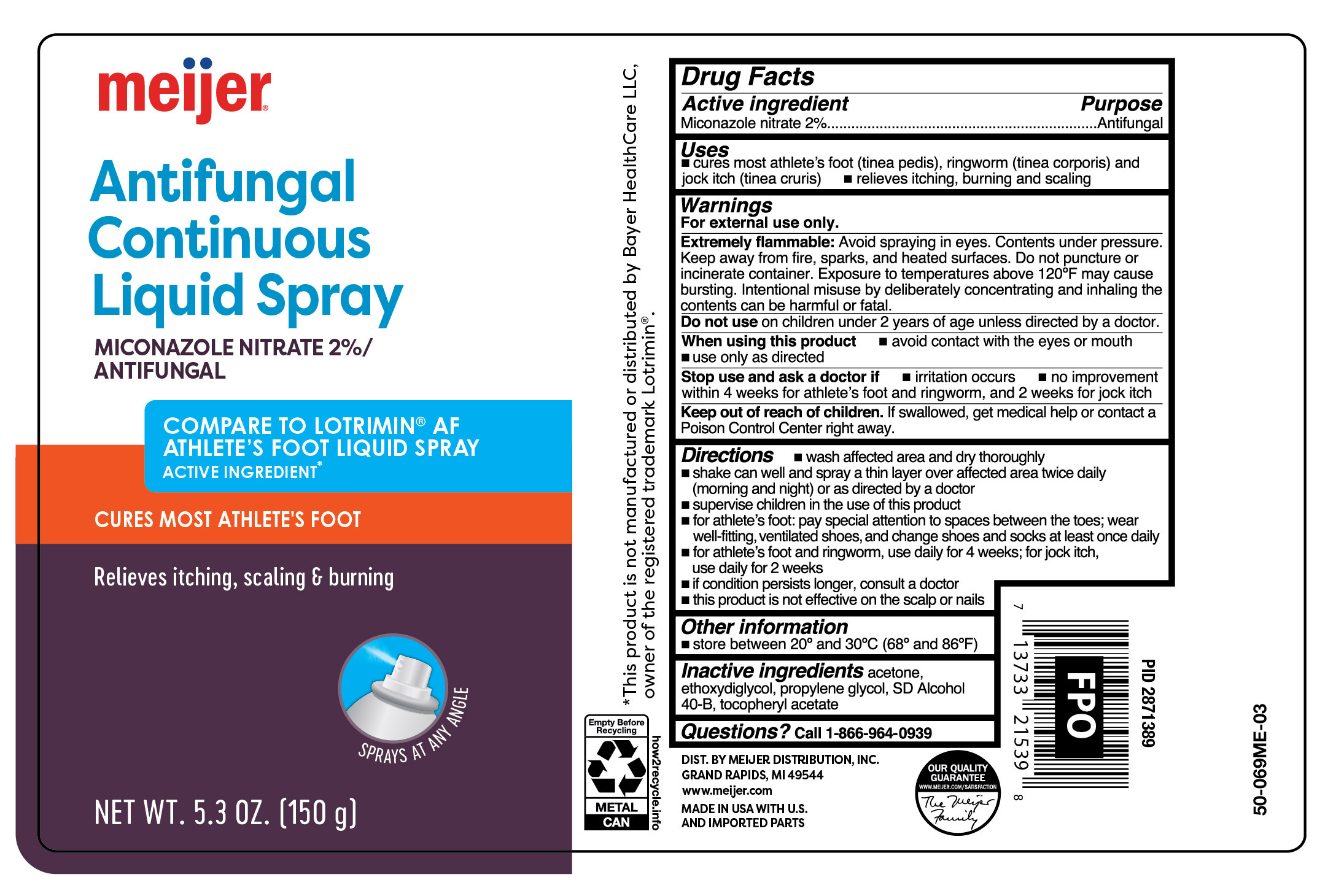 DRUG LABEL: Antifungal Miconazole Liquid Continuous
NDC: 79481-0599 | Form: AEROSOL, SPRAY
Manufacturer: Meijer Distribution Inc
Category: otc | Type: HUMAN OTC DRUG LABEL
Date: 20251030

ACTIVE INGREDIENTS: MICONAZOLE NITRATE 20 mg/1 g
INACTIVE INGREDIENTS: ACETONE; DIETHYLENE GLYCOL MONOETHYL ETHER; PROPYLENE GLYCOL; ALCOHOL; .ALPHA.-TOCOPHEROL ACETATE

Meijer Antifungal Miconazole Liquid Continuous Spray

Active ingredient

Miconazole nitrate 2%

Purpose

Antifungal

Uses

- cures most athlete's foot (tinea pedis), ringworm (tinea corporis) and jock itch (tinea cruris)
- relieves itching, burning and scaling

Warnings

For external use only.

Extremely flammable:

Contents under pressure. Keep away from fire, sparks, and heated surfaces. Do not puncture or incinerate container. Exposure to temperatures above 120°F may cause bursting. Intentional misuse by deliberately concentrating and inhaling the contents can be harmful or fatal.

When using this product

- avoid contact with the eyes or mouth
- use only as directed

Stop use and ask a doctor if

- irritation occurs
- no improvement within 4 weeks for athlete's foot and ringworm, and 2 weeks for jock itch

Keep out of reach of children.

If swallowed, get medical help or contact a Poison Control Center right away.

Directions

- wash affected area and dry thoroughly
- shake can well and spray a thin layer over affected area twice daily (morning and night) or as directed by a doctor
- supervise children in the use of this product
- for athlete's foot: pay special attention to spaces between the toes; wear well-fitting, ventilated shoes, and change shoes and socks at least once daily
- for athlete's foot and ringworm, use daily for 4 weeks; for jock itch, use daily for 2 weeks
- if condition persists longer, consult a doctor
- this product is not effective on the scalp or nails

Other information

store between 20º and 30ºC (68ºF and 86ºF)

Inactive ingredients

acetone, ethoxydiglycol, propylene glycol, SD alcohol 40-B (74%w/w), tocopheryl acetate

Questions?

Call 1-866-964-0939

Principal Display Panel

meijer

MEDICATED

athlete's foot

Miconazole Nitrate | Antifungal

Liquid Spray

CONTINUOUS

Cures most athlete's foot

Relieves itching, scaling & burning

NET WT 5.3 OZ (150 g)